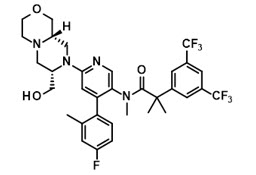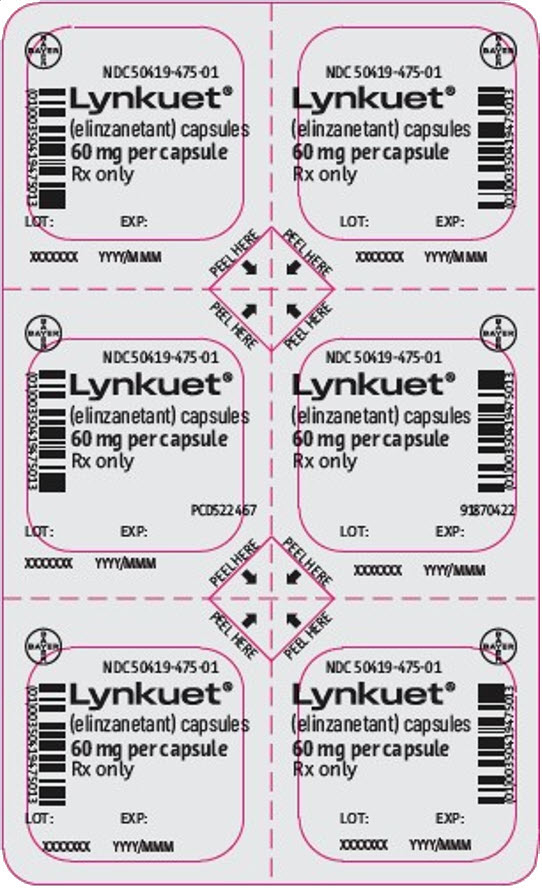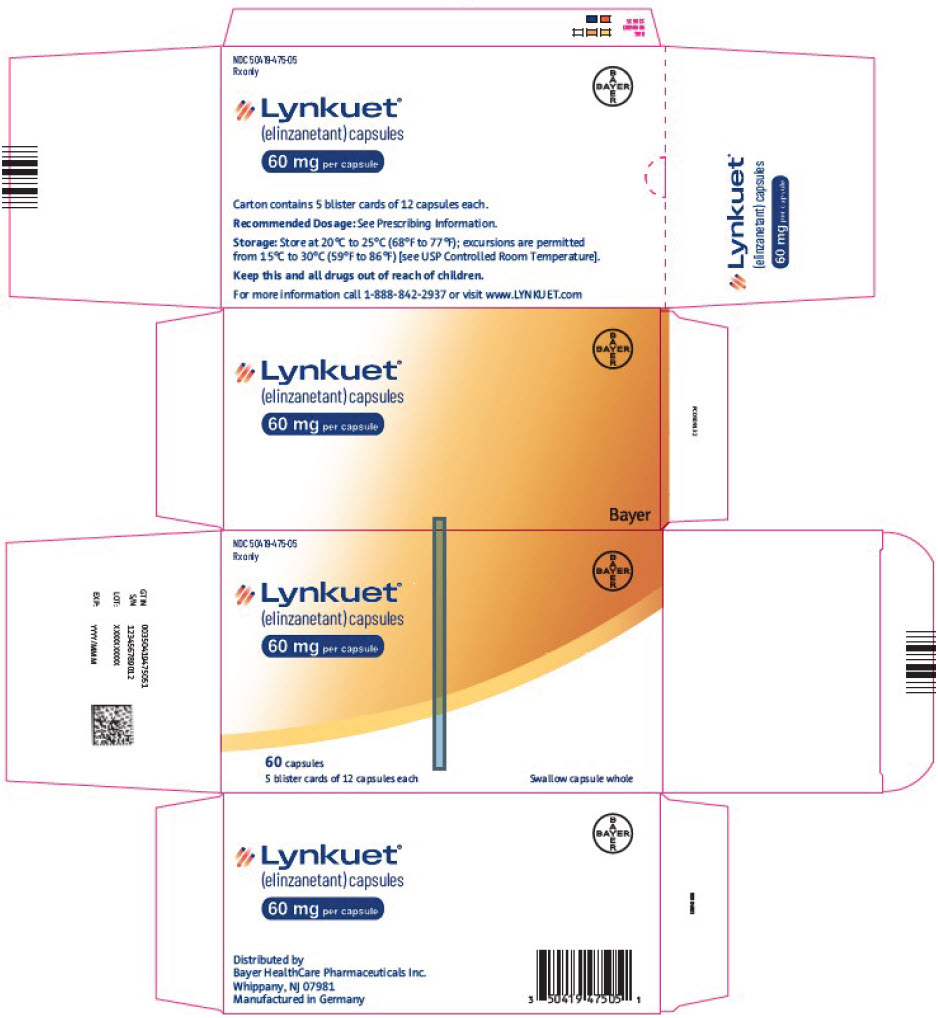 DRUG LABEL: LYNKUET
NDC: 50419-475 | Form: CAPSULE
Manufacturer: Bayer HealthCare Pharmaceuticals Inc.
Category: prescription | Type: HUMAN PRESCRIPTION DRUG LABEL
Date: 20251028

ACTIVE INGREDIENTS: ELINZANETANT 60 mg/1 1
INACTIVE INGREDIENTS: .ALPHA.-TOCOPHEROL; CAPRYLOCAPROYL POLYOXYLGLYCERIDES, UNSPECIFIED; GLYCERYL MONOOLEATE; GLYCERYL MONOCAPRYLOCAPRATE; POLYSORBATE 80; FERRIC OXIDE RED; FERRIC OXIDE YELLOW; GELATIN, UNSPECIFIED; SORBITOL; GLYCERIN; TITANIUM

HIGHLIGHTS OF PRESCRIBING INFORMATION

These highlights do not include all the information needed to use LYNKUET safely and effectively. See full prescribing information for LYNKUET.
LYNKUET® (elinzanetant) capsules, for oral use
Initial U.S. Approval: 2025

1 INDICATIONS AND USAGE

LYNKUET is a neurokinin 1 (NK1) and neurokinin 3 (NK3) receptor antagonist indicated for the treatment of moderate to severe vasomotor symptoms due to menopause. (1)

2 DOSAGE AND ADMINISTRATION

The recommended dosage is 120 mg (two 60 mg capsules) orally once daily at bedtime with or without food. (2.2)

Swallow capsules whole. Do not cut, crush, or chew capsules. (2.2)

See full prescribing information for LYNKUET dosage modification due to drug interactions. (2.3)

3 DOSAGE FORMS AND STRENGTHS

Capsules: 60 mg (3)

4 CONTRAINDICATIONS

- Pregnancy. (4)

5 WARNINGS AND PRECAUTIONS

- CNS Depressant Effect and Daytime Impairment: Advise patients about the potential for somnolence and other nervous system effects. Advise patients who experience these effects to refrain from driving or engaging in hazardous occupations or activities until the effects have resolved (5.1)
- Hepatic Transaminase Elevations: Perform bloodwork prior to initiation of LYNKUET to evaluate for hepatic function and injury. Do not start therapy if serum transaminase concentration is equal to or exceeds two times the upper limit of normal (ULN). Perform follow-up evaluations of hepatic transaminase concentration 3 months after initiation. Do not start therapy if serum transaminase concentration is equal to or exceeds two times the ULN or if the total bilirubin is equal to or exceeds two times the ULN. Advise patients to discontinue LYNKUET immediately in case of signs or symptoms suggesting liver injury. (5.2)
- Risk of pregnancy loss: May cause pregnancy loss or stillbirth when administered during pregnancy. Exclude pregnancy in females of reproductive potential prior to initiating LYNKUET. Discontinue if pregnancy is confirmed (5.3)
- Risk of seizures in patients with a history of seizures (5.4)

6 ADVERSE REACTIONS

The most frequently reported (≥5%) adverse reactions were headache, fatigue, dizziness and somnolence. (6.1)

To report SUSPECTED ADVERSE REACTIONS, contact Bayer HealthCare Pharmaceuticals Inc. at 1-888-842-2937 or FDA at 1-800-FDA-1088 or www.fda.gov/medwatch.

7 DRUG INTERACTIONS

- Strong CYP3A4 Inhibitors and grapefruit (juice): Avoid concomitant use with LYNKUET. (7.1)
- Moderate CYP3A4 Inhibitors: Reduce LYNKUET dosage to 60 mg once daily. (2.2, 7.1)
- Strong and Moderate CYP3A4 Inducers: Avoid concomitant use with LYNKUET. (7.1)

8 USE IN SPECIFIC POPULATIONS

- End Stage Renal Disease with or without hemodialysis: Not recommended. (8.6)
- Moderate to Severe Hepatic Impairment: Not recommended. (8.7)

FULL PRESCRIBING INFORMATION

1 INDICATIONS AND USAGE

LYNKUET is indicated for the treatment of moderate to severe vasomotor symptoms (VMS) due to menopause.

2 DOSAGE AND ADMINISTRATION

2.1 Recommended Evaluation and Testing Before Initiation of LYNKUET

- Exclude pregnancy in females of reproductive potential [see Contraindications (4)], Warnings and Precautions (5.3), and Use in Specific Populations (8.3)].
- Perform baseline hepatic laboratory tests to evaluate for hepatic function and injury [including serum alanine aminotransferase (ALT), serum aspartate aminotransferase (AST), serum alkaline phosphatase (ALP), and serum bilirubin (total and direct)] before initiating treatment with LYNKUET. Do not start LYNKUET if ALT or AST is ≥ 2 times upper limit of normal (ULN) or if the total bilirubin is ≥ 2 times ULN [see Warnings and Precautions (5.2) and Use in Specific Populations (8.7)].

2.2 Recommended Dosage

The recommended dosage of LYNKUET is 120 mg (two 60 mg capsules) orally once daily at bedtime at about the same time each day. If a dose is missed at bedtime, take the next dose as scheduled on the following day. Do not take two doses on the same day to make up for a missed dose.

Take LYNKUET with or without food. Take LYNKUET with water and swallow capsules whole. Do not cut, crush or chew capsules.

2.3 Dosage Modifications for Drug Interactions

Dosage modifications for concomitant use with specific drugs are provided in Table 1 [see Drug Interactions (7.1)].

Table 1. Dosage Modifications for Drug Interactions
Concomitant Drug | LYNKUET Dosage
Strong CYP3A4 inhibitors and grapefruit (juice) | Avoid concomitant use
Moderate CYP3A4 inhibitors | 60 mg (one capsule) orally once daily at bedtime [see Storage and Handling (16.2)].
 | After discontinuation of the moderate CYP3A4 inhibitor (after 3 to 5 half-lives of the inhibitor), LYNKUET should be used at the usual dosage of 120 mg once daily.
Strong and Moderate CYP3A4 inducers | Avoid concomitant use

3 DOSAGE FORMS AND STRENGTHS

Capsules: 60 mg, opaque red, oblong, soft, gelatin capsules, with white printing of "EZN60".

4 CONTRAINDICATIONS

LYNKUET is contraindicated in pregnancy. Exposure to LYNKUET may cause pregnancy loss or stillbirth when administered during pregnancy [see Use in Specific Populations (8.1, 8.3)].

5 WARNINGS AND PRECAUTIONS

5.1 Central Nervous System (CNS) Depressant Effect and Daytime Impairment

In the three OASIS trials, nervous system effects (including somnolence, fatigue, vertigo, dizziness and presyncope) occurred in 11.9% of patients on LYNKUET compared to 3.5% on placebo. [see also Adverse Reactions (6.1)].

Advise patients about the potential for somnolence and other nervous system effects. Advise patients who experience these effects to refrain from driving or engaging in hazardous occupations or activities until the effects have resolved [see Clinical Studies (14.3)].

5.2 Hepatic Transaminase Elevations

Elevations in serum transaminase (ALT and/or AST) concentrations equal to or greater than three times the ULN occurred in 0.6% of patients receiving LYNKUET and 0.4% of patients receiving placebo up to 12 weeks in three clinical trials. Perform baseline bloodwork (including ALT, AST, alkaline phosphatase, and total and direct bilirubin) prior to initiation of LYNKUET to evaluate for hepatic function and injury. Do not start therapy if serum transaminase concentration is equal to or exceeds two times the ULN or if the total bilirubin is equal to or exceeds two times the ULN. Perform follow-up evaluations of hepatic transaminase concentration 3 months after initiation of therapy.

Advise patients to discontinue LYNKUET immediately and seek medical attention including hepatic laboratory tests if they experience signs or symptoms that may suggest liver injury (new onset fatigue, decreased appetite, nausea, vomiting, pruritus, jaundice, pale feces, dark urine, or abdominal pain).

Discontinue LYNKUET if transaminase elevations exceed five times the ULN or if transaminase elevations exceed three times the ULN and total bilirubin exceeds two times the ULN.

Exclude alternative causes of hepatic laboratory test elevations.

5.3 Risk of Pregnancy Loss

LYNKUET is contraindicated for use in pregnancy [see Contraindications (4)]. Findings from animal studies suggest that LYNKUET can cause pregnancy loss or stillbirth. Exclude pregnancy in females of reproductive potential prior to initiating LYNKUET. Advise females of reproductive potential to use effective contraception during treatment with LYNKUET and for 2 weeks after stopping LYNKUET [see Use in Specific Populations (8.1, 8.3)].

5.4 Risk of Seizures in Patients with History of Seizures

Seizure was reported in one patient with a history of seizures in the clinical trials of LYNKUET. In addition, convulsions were observed in studies conducted in male and female rats [see Nonclinical Toxicology (13.2)]. Use LYNKUET with caution in patients with a history of seizures or with conditions that potentially lower the seizure threshold.

6 ADVERSE REACTIONS

The following clinically significant adverse reactions are described elsewhere in the labeling:

- Central Nervous System (CNS) Depressant Effect and Daytime Impairment [see Warnings and Precautions (5.1)]
- Hepatic Transaminase Elevations [see Warnings and Precautions (5.2)]

6.1 Clinical Trials Experience

Because clinical trials are conducted under widely varying conditions, adverse reaction rates observed in the clinical trials of a drug cannot be directly compared to rates in the clinical trials of another drug and may not reflect the rates observed in clinical practice.

The safety of LYNKUET was evaluated in three randomized, double-blind, placebo-controlled, multicenter clinical trials (OASIS 1, OASIS 2, OASIS 3) in 1420 women. In OASIS 1 and OASIS 2 combined, 793 women received LYNKUET or placebo for 12 weeks. After the first 12 weeks, 341 women randomized to LYNKUET continued to receive LYNKUET for another 14 weeks, with a total treatment duration of up to 26 weeks. In OASIS 1 and OASIS 2 combined, 349 women received placebo for the first 12 weeks and 348 women switched to LYNKUET for the next 14 weeks. In OASIS 3, 627 women received LYNKUET or placebo for up to 52 weeks to evaluate long-term safety [see Clinical Studies (14)].

Common Adverse Reactions

In OASIS 1 and 2 combined, through the first 12 weeks, commonly reported adverse reactions in the LYNKUET group (≥2% and greater than in placebo) were headache, fatigue, gastroesophageal reflux disease, dizziness, nausea, and somnolence.

Similar adverse reactions were seen in OASIS 3. Table 2 shows adverse reactions reported in at least 2% of women and more commonly in women taking LYNKUET than placebo in OASIS 3.

Table 2. Common Adverse Reactions Reported in ≥ 2% in LYNKUET and Greater than Placebo, Weeks 1-52 (OASIS 3)
Adverse Reaction | LYNKUET N=313 n (%) | Placebo N=314 n (%)
Headache | 30 (9.6) | 22 (7.0)
Fatigue [Includes asthenia.] | 23 (7.3) | 9 (2.9)
Dizziness [Includes balance disorder, presyncope, vertigo, vertigo CNS origin, vertigo positional, and vestibular neuronitis.] | 19 (6.1) | 6 (1.9)
Somnolence [Includes lethargy.] | 16 (5.1) | 4 (1.3)
Abdominal pain [Includes abdominal discomfort, abdominal pain lower/upper.] | 14 (4.5) | 8 (2.5)
Rash [Includes dermatitis, urticaria.] | 13 (4.2) | 5 (1.6)
Diarrhea | 12 (3.8) | 3 (1.0)
Muscle spasms [Includes muscle tightness.] | 10 (3.2) | 2 (0.6)

Adverse Reactions Leading to Discontinuation

In OASIS 3, adverse reactions leading to treatment discontinuation (≥1% in LYNKUET and greater than placebo) were abdominal pain (1.6%), fatigue (1.6%), depression (1.6%) and headache (1.3%).

Photosensitivity

In the OASIS trials, mild to moderate events of photosensitivity occurred in 0.5% of patients receiving LYNKUET and 0.1% of patients receiving placebo. Onset of photosensitivity reactions ranged from day 1 to day 290. While discontinuation occurred in one patient, photosensitivity events in other patients resolved under continued treatment with LYNKUET [see Nonclinical Toxicology (13.2)].

7 DRUG INTERACTIONS

7.1 Effects of Other Drugs on LYNKUET

Elinzanetant is primarily metabolized via CYP3A4 enzyme. Table 3 describes drug interactions where concomitant use of another drug affects LYNKUET.

Table 3: Drug Interactions: Concomitant Use of Other Drugs Affect the Use of LYNKUET
Strong and Moderate CYP3A4 Inhibitors [See www.fda.gov/CYPandTransporterInteractingDrugs for examples of strong and moderate CYP3A4 inhibitors, and CYP3A4 inducers.]
Prevention or Management | Strong CYP3A4 Inhibitors and grapefruit (juice): Avoid concomitant use.
 | Moderate CYP3A4 Inhibitors: Reduce the LYNKUET dosage [see Dosage and Administration (2.2)].
Clinical Effect(s) | Strong and moderate CYP3A4 inhibitors increase elinzanetant exposure, which may increase the risk of LYNKUET-associated adverse reactions [see Clinical Pharmacology (12.3)].
Strong and Moderate CYP3A4 Inducers
Prevention or Management | Strong and moderate CYP3A4 inducers: Avoid concomitant use.
Clinical Effect(s) | Strong and moderate CYP3A4 inducers decrease elinzanetant exposure, which may reduce the effectiveness of LYNKUET.

7.2 Effects of LYNKUET on Other Drugs

CYP3A4 Substrates

Avoid concomitant use unless otherwise recommended in the Prescribing Information for CYP3A4 substrates where minimal concentration changes may lead to serious adverse reactions. See www.fda.gov/CYPandTransporterInteractingDrugs for examples of CYP3A4 substrates.

Elinzanetant is a weak inhibitor of CYP3A4. Concomitant use of LYNKUET increases exposure of CYP3A4 substrates [see Clinical Pharmacology (12.3)], which may increase the risk of adverse reactions related to these substrates.

8 USE IN SPECIFIC POPULATIONS

8.1 Pregnancy

Risk Summary

LYNKUET is contraindicated in pregnancy [see Contraindications (4)]. If pregnancy occurs during the use of LYNKUET, discontinue treatment. Based on findings from animal reproduction studies, LYNKUET may cause pregnancy loss or stillbirth but not fetal malformations when administered during pregnancy. There are no data on the use of LYNKUET in pregnant women to evaluate for a drug-associated risk of major birth defects, miscarriage, or adverse maternal or fetal outcomes.

In animal reproduction studies in rats, an increase in total litter loss or stillbirth and a decrease of neonatal pup viability was observed within the range of human therapeutic exposure when dams were treated orally throughout gestation and lactation [i.e., gestation day 6 to lactation day 21]. There was an increase in percentage of pre- and post-implantation embryo loss and decrease in fetal body weights at 16-fold the human therapeutic exposure when rat dams were treated orally prior to mating and through the early embryonic period [i.e., 22 days before mating to post-coitum day 6]. In rabbits, there was marked body weight loss and decreased food consumption in dams treated orally during gestation day 7 to 19 at doses equivalent to human therapeutic exposure (see Data).

Data

Animal Data

In a fertility and early embryonic development study in female rats, once daily oral doses of elinzanetant were administered 22 days before mating through post-coitum day 6. Increased percentage of pre-implantation and post-implantation embryo loss, resulting in reduced litter size, and lower fetal body weights were seen at the dose of 100 mg/kg/day (14-fold the AUC(0-24) at the human therapeutic dose). These effects were not observed following dosing at 25 mg/kg/day (3-fold the AUC(0-24) at the human therapeutic dose).

In an embryo-fetal development study in pregnant rats, once daily oral doses of elinzanetant were administered throughout organogenesis from gestation day 6 to 17. No evidence of embryo-fetal lethality or teratogenicity occurred at doses ≤100 mg/kg/day (23-fold the AUC(0-24) at the human therapeutic dose) and no maternal toxicity occurred at doses ≤25 mg/kg/day (7-fold the AUC(0-24) at the human therapeutic dose).

In an embryo-fetal development study in pregnant rabbits, twice daily oral doses of elinzanetant were administered throughout organogenesis from gestation day 7 to 19. Maternal toxicity in the form of marked body weight loss and decreased food consumption leading to early sacrifice in 4 out of 27 females was observed at the highest tested dose of 140 mg/kg/day (equivalent to the AUC(0-24) at the human therapeutic dose). No evidence of embryo-fetal lethality or teratogenicity occurred in fetuses of surviving dams at doses ≤140 mg/kg/day (equivalent to the AUC(0-24) at the human therapeutic dose).

In a pre- and post-natal development study in rats, once daily oral doses of elinzanetant were administered from gestation day 6 to lactation day 21. A higher incidence of still born pups, an increase in total litter loss, a decrease in pup viability between postnatal days 0 and 4, and an increase in the number of neonatal pups without milk in the stomach were observed at a dose of ≥5 mg/kg/day (equivalent to the AUC(0-24) at the human therapeutic dose).

8.2 Lactation

Risk Summary

There are no data on the presence of elinzanetant or its metabolites in human milk, the effects on the breastfed child, or the effects on milk production. Elinzanetant is present in animal milk. When a drug is present in animal milk, it is likely that the drug will be present in human milk (see Data).

Data

Animal Data

Following administration of radiolabeled elinzanetant to lactating rats, approximately 6% of the elinzanetant dose was excreted in the milk.

Principle human metabolites of elinzanetant were also detected in the plasma of pups from rat dams that were dosed once daily orally during pregnancy and lactation at ≥1.5 mg/kg/day (elinzanetant AUC(0-24) below the range of human therapeutic exposure).

8.3 Females and Males of Reproductive Potential

Based on findings from animal reproduction studies, LYNKUET may cause pregnancy loss or stillbirth when administered during pregnancy. Fetal malformations were not observed in those studies [see Use in Specific Populations (8.1)].

Pregnancy Testing

Exclude pregnancy before initiating treatment with LYNKUET. Perform pregnancy testing if pregnancy is suspected during treatment with LYNKUET, and discontinue treatment if pregnancy is confirmed [see Contraindications (4) and Warnings and Precautions (5.3)].

Contraception

Females

Pregnancy should be prevented in women of reproductive potential by using effective contraception during and for 2 weeks after stopping treatment because LYNKUET can cause pregnancy loss or stillbirth [see Use in Specific Populations (8.1)].

8.4 Pediatric Use

The efficacy and safety of LYNKUET in pediatric patients have not been established, and LYNKUET is not indicated in this population.

8.5 Geriatric Use

There have not been sufficient numbers of geriatric women involved in clinical trials utilizing LYNKUET to determine whether those over 65 years of age differ from younger women in their response to LYNKUET.

8.6 Renal Impairment

No dose adjustment is required for patients with mild to severe [estimated glomerular filtration rate (eGFR) 15 to < 90 mL/min] renal impairment. The effect of end-stage renal disease (eGFR <15 mL/min) (with or without hemodialysis) on the pharmacokinetics of LYNKUET has not been studied [see Clinical Pharmacology (12.3)].

8.7 Hepatic Impairment

No dose adjustment is required in patients with mild (Child-Pugh A) hepatic impairment. Moderate (Child-Pugh B) hepatic impairment increased the exposure of LYNKUET. LYNKUET has not been studied in individuals with severe (Child-Pugh C) hepatic impairment. LYNKUET is not recommended in patients with moderate or severe hepatic impairment [see Clinical Pharmacology (12.3)].

10 OVERDOSAGE

There is no specific antidote for LYNKUET. In the case of overdose, the individual should be closely monitored, and supportive treatment should be considered based on signs and symptoms.

11 DESCRIPTION

LYNKUET is an NK1 and NK3 receptor antagonist.

The chemical name of elinzanetant is 2-[3,5-bis(trifluoromethyl)phenyl]-N-{4-(4-fluoro-2-methylphenyl)-6-[(7S,9aS)-7-(hydroxymethyl)hexahydropyrazino[2,1-c][1,4]oxazin-8(1H)-yl]pyridin-3-yl}-N,2-dimethylpropanamide having a molecular formula of C33H35F7N4O3 and a molecular weight of 668.7.

The structural formula of elinzanetant is:

Elinzanetant is a white to yellowish powder and is practically insoluble in water and slightly soluble under acidic conditions.

Each LYNKUET (elinzanetant) capsule for oral use contains 60 mg of elinzanetant and the following inactive ingredients: all-rac-α-Tocopherol, caprylocaproyl macrogolglycerides, glycerol monocaprylocaprate, glycerol mono-oleate, and polysorbate 80. The capsule is composed of edible ink, ferric oxide red, ferric oxide yellow, gelatin, sorbitol special-glycerin, and titanium dioxide.

12 CLINICAL PHARMACOLOGY

12.1 Mechanism of Action

LYNKUET is a neurokinin 1 (NK1) and neurokinin 3 (NK3) receptor antagonist. Inhibition of Substance P and Neurokinin B through antagonism of NK1 and NK3 receptor signaling on kisspeptin/neurokinin B/dynorphin (KNDy) neurons can modulate neuronal activity in thermoregulation associated with hot flashes.

Elinzanetant has higher affinity for human NK1 receptors (pKi values of 8.7 to 10.2) and NK3 receptors (pKi values of 8.0 to 8.8) than for human NK2 receptors (pKi values of approximately 6.0).

12.2 Pharmacodynamics

Cardiac Electrophysiology

No clinically relevant prolongation of the QTc interval was observed after single oral administration of elinzanetant at doses up to 5 times the maximum recommended dose. However, QTc prolongation effect of elinzanetant when co-administered with strong CYP3A4 inhibitors has not been sufficiently characterized.

12.3 Pharmacokinetics

Elinzanetant Cmax and AUC increased in a greater than dose-proportional manner (20% to 50%) over the dose range from 40 to 160 mg once daily (0.33 to 1.33 times the highest recommended dose).

Elinzanetant steady state plasma concentrations were reached in 5 to 14 days after daily dosing.

Elinzanetant accumulation is <2-fold at the approved recommended dosage.

Absorption

Elinzanetant median (min-max) time to maximum plasma concentration (Tmax) is 1.0 hours (1-2.5 hours) at steady state. Elinzanetant absolute bioavailability is 52% following oral administration.

Effect of Food

No clinically significant differences in elinzanetant pharmacokinetics were observed following administration with a high-calorie, high-fat meal containing approximately 1000 calories (500-600 calories from fat, 250 calories from carbohydrates, and 150 calories from protein).

Distribution

The mean volume of distribution after intravenous administration at steady state of elinzanetant is 137 L. The plasma protein binding of elinzanetant is 99.7%. The blood-to-plasma ratio is between 0.6 and 0.7.

Elimination

Elinzanetant elimination half-life was approximately 45 hours in women with vasomotor symptoms. The clearance of elinzanetant after a single intravenous dose was 8.77 L/h.

Metabolism

Elinzanetant is primarily metabolized by CYP3A4 to yield three major active metabolites, M18/21, M27, and M30/34. These metabolites have similar potency for the human NK1 and NK3 receptors as compared to elinzanetant. The ratio of these metabolites to parent in plasma is approximately 0.39.

Excretion

Following a single oral dose of radiolabeled elinzanetant in healthy subjects, approximately 90% of the dose was recovered in feces (50% unchanged) and less than 1% with urine.

Specific Populations

No clinically significant differences in the pharmacokinetics of LYNKUET were observed based on race.

Patients with Renal Impairment

In patients with mild (eGFR 60 to <90 mL/min) renal impairment, mean elinzanetant Cmax increased 1.9-fold and AUC increased 1.6-fold. In patients with moderate (eGFR 30 to <60 mL/min) renal impairment, mean elinzanetant Cmax increased 1.8-fold and AUC increased 1.7-fold. In patients with severe (eGFR< 30 mL/min) renal impairment, mean elinzanetant Cmax increased 1.2-fold and AUC increased 1.1-fold.

Population pharmacokinetic analysis of the clinical trial data indicate similar exposure of elinzanetant in patients with mild and moderate renal impairment compared to patients with normal renal function.

Elinzanetant has not been studied in patients with end-stage renal disease (eGFR <15 mL/min) [see Use in Specific Populations (8.7)].

Patients with Hepatic Impairment

In patients with Child-Pugh Class A (mild) hepatic impairment, mean elinzanetant Cmax increased 1.2-fold and AUC(0-24) increased 1.5-fold. In patients with Child-Pugh Class B (moderate) hepatic impairment, mean elinzanetant Cmax and AUC(0-24) increased by 2.3-fold.

Elinzanetant has not been studied in patients with Child-Pugh Class C (severe) hepatic impairment [see Use in Specific Populations (8.6)].

Drug Interaction Studies

Clinical Studies and Model-Informed Approaches

No clinically significant differences in elinzanetant pharmacokinetics were observed when used concomitantly with esomeprazole (proton pump inhibitor). No clinically significant differences in the pharmacokinetics of the following oral drugs were observed when used concomitantly with elinzanetant: tamoxifen (substrate of CYP2D6, CYP3A4 and P-gp) and rosuvastatin (substrate of BCRP, OATP1B1/OATP1B3, and OAT3).

Strong CYP3A4 and P-gp inhibitors: Elinzanetant Cmax increased approximately 3.3-fold and AUC increased 6.3-fold following concomitant use with itraconazole 200 mg (strong CYP3A4 and P-gp inhibitor).

Moderate CYP3A4 Inhibitors: Elinzanetant Cmax and AUC are predicted to increase 2.0-fold and 3.0-fold, respectively, following concomitant use of elinzanetant 120 mg with erythromycin (moderate CYP3A4 inhibitor). PBPK predictions after co-administration of 60 mg elinzanetant [(see Dosage and Administration (2.3)] with the moderate CYP3A4 inhibitor erythromycin showed a 1.4-fold increase of elinzanetant AUC and no increase for Cmax when compared to 120 mg, the regular recommended elinzanetant dosage.

Weak CYP3A4 Inhibitors: Elinzanetant Cmax is predicted to increase 1.3-fold and AUC increase 1.5-fold following concomitant use with cimetidine (weak CYP3A4 inhibitor).

Moderate to Strong CYP3A4 Inducers: Elinzanetant Cmax reduced by 44% and AUC reduced by 64% following concomitant use with carbamazepine (moderate to strong CYP3A4 inducer) 600 mg administered twice daily.

Sensitive CYP3A4 Substrates: Elinzanetant increased midazolam (sensitive CYP3A4 substrate) Cmax 1.5-fold and AUC 1.8-fold.

In Vitro Studies

Cytochrome P450 (CYP450) Enzymes: Elinzanetant and its metabolites M18/21, M27, and M30/M34 inhibited CYP3A4 but did not inhibit CYP1A1, 1A2, 2A6, 2B6, 2C8, 2C9, 2C19, 2D6, 2E1, or 2J2, or induce CYP1A2, 2B6, 2C19, or 3A4 at clinically relevant concentrations.

Transporter systems: Elinzanetant is a substrate for P-gp but not for OATP1A2, OATP2B1, BCRP, OATP1B1, OATP1B3, or MRP4. Elinzanetant and its metabolites M18/21, M27, and M30/M34 inhibited P-gp, BCRP, and BSEP in vitro but did not inhibit OAT1, OAT3, OCT1, OCT2, MATE2-K, or MRP2.

13 NONCLINICAL TOXICOLOGY

13.1 Carcinogenesis, Mutagenesis, Impairment of Fertility

Carcinogenesis

In a 2-year carcinogenicity study in female rats, oral doses of elinzanetant ≥60 mg/kg/day (29-fold the total AUC(0-24) at the human therapeutic dose) increased the incidence of endometrial adenocarcinoma, the combination of malignant and benign endometrial tumors and squamous cell carcinoma of the uterus, and lymphomas of the hematolymphoid system. These effects were not observed at a dose representing 7-fold the total AUC(0-24) at the human therapeutic dose. The clinical significance of these findings is unknown.

In a 26-week carcinogenicity study in rasH2 transgenic mice, there was no evidence of drug-related carcinogenicity at 85 or 70 mg/kg/day in males or females, respectively.

Mutagenesis

Elinzanetant showed no genotoxic potential in bacterial mutation assay (Ames test), mouse lymphoma assay, and in-vivo bone marrow micronucleus test in rats. Additionally, the principal human metabolites of elinzanetant were negative for genotoxicity in vitro in the Ames and micronucleus test.

13.2 Animal Toxicology and/or Pharmacology

Repeat dose toxicity studies were conducted in rats and cynomolgus monkeys. The findings of clinical relevance are described below:

Reproductive organs (female)

In female rats, daily oral administration of elinzanetant for 4 weeks at 100 mg/kg (40-fold the AUC(0-24) at the human therapeutic dose) induced mucification of the vaginal epithelium, uterine atrophy, and persistent corpora lutea. In monkeys, twice daily oral administration of elinzanetant for 39 weeks at doses ≥60 mg/kg/day (2-fold the human therapeutic exposure) reduced cyclical ovarian activity.

Central Nervous System (CNS)

In male and female rats, twice daily oral administration of elinzanetant for 13 weeks induced involuntary muscle contractions starting around treatment day 24 and convulsions starting around day 34, when exposures in male and female rats were estimated to be ≥4-fold the AUC(0-24) at the human therapeutic dose.

In female rats, twice daily oral administration of elinzanetant for 2 years induced convulsions starting around treatment day 106, when exposures were estimated to be ≥17-fold the AUC(0-24) at the human therapeutic dose.

Skeletal muscle

In rats, twice daily oral administration of elinzanetant for 13 weeks at ≥100 mg/kg/day (equivalent to ≥16-fold the AUC(0-24) at human therapeutic dose) induced skeletal muscle degeneration and necrosis. These findings were not related to the convulsions presented by elinzanetant-treated rats in the same 13-week toxicity study (described under CNS above). A longer duration (26-week) toxicity study in rats as well as a follow up mechanistic study in male rats did not have any skeletal muscle findings. The clinical relevance of these findings is unknown.

Gastrointestinal system

In male and female monkeys, once daily oral administration of elinzanetant for 4 weeks at 60 mg/kg/day (4-fold the AUC(0-24) at human therapeutic exposure) caused loose/watery fecal consistency and reduced food intake. In three studies of male and female monkeys treated orally with elinzanetant for 13 to 39 weeks, gastrointestinal disturbances characterized by diarrhea were observed at doses ≥30 mg/kg/day (0.2-fold the AUC(0-24) at human therapeutic exposure). Diarrhea eventually led to dehydration, weight loss, and general ill-health in animals at doses of ≥60 mg/kg/day.

Photosensitivity

An in-vitro study demonstrated that elinzanetant has some potential for photosensitization. While studies of photosensitivity in animals were not conducted, there is evidence that elinzanetant distributes to and accumulates in melanin-containing tissues in the rats.

14 CLINICAL STUDIES

14.1 Effects on Vasomotor Symptoms (VMS) in Postmenopausal Women

The efficacy of LYNKUET for the treatment of moderate to severe vasomotor symptoms due to menopause was demonstrated in the first 12 weeks of two randomized, double-blind, placebo-controlled, multicenter clinical trials. In OASIS 1 (NCT05042362) and OASIS 2 (NCT05099159), 796 menopausal women were randomized 1:1 to receive LYNKUET 120 mg or placebo once daily at bedtime for 12 weeks. In each of these two trials, after the first 12 weeks, women on placebo were switched over to LYNKUET and all women were then treated with LYNKUET for a 14-week extension for up to 26 weeks total exposure. Women who had at least 50 moderate to severe hot flashes (HFs), including night-time HFs, per week, were enrolled in OASIS 1 and 2. In these trials, postmenopausal status was defined as at least 12 months of spontaneous amenorrhea, or at least 6 months of spontaneous amenorrhea with serum follicle stimulating hormone levels >40 mIU/mL and a serum estradiol concentration of <30 pg/mL, or at least 6 months after hysterectomy with serum follicle-stimulating hormone >40 mIU/mL and serum estradiol <30 pg/mL, or at least 6 weeks post-surgical bilateral oophorectomy with or without hysterectomy.

In OASIS 1 and OASIS 2, the mean age of women was 54.6 years (range 40-65). The racial distribution was 80.4% White, 17.1% Black or African American, and 0.5% Asian. About 8.5 % women were of Hispanic or Latino ethnicity. The study population included women with prior hysterectomy (38.8%), prior uni-/bilateral oophorectomy (20.6%), or prior menopausal hormone therapy (MHT) use (31.4%).

The primary efficacy endpoints in both trials were the mean change in frequency and severity of moderate to severe vasomotor symptoms from baseline to Weeks 4 and 12, including day and night HFs measured using the Hot Flash Daily Diary (HFDD). In both trials, LYNKUET treatment groups showed statistically significant and clinically meaningful reduction (≥ 2 hot flashes over 24 hours) in the frequency of moderate to severe HFs from baseline to Weeks 4 and 12 compared to placebo. In both trials, LYNKUET treatment groups showed a statistically significant reduction in severity of moderate to severe vasomotor symptoms from baseline to Weeks 4 and 12 compared to placebo. Results of the co-primary endpoints for change from baseline to Weeks 4 and 12 in mean frequency and severity of moderate to severe vasomotor symptoms over 24 hours from OASIS 1 and OASIS 2 are shown in Tables 4 and 5.

Table 4: Mean Baseline and Mean Change in Frequency of Moderate to Severe VMS over 24 hours from Baseline to Weeks 4 and 12 (OASIS 1 and 2)
 | OASIS 1 |  | OASIS 2
Parameter | LYNKUET 120 mg (N= 199) | Placebo (N= 197) | LYNKUET 120 mg (N= 200) | Placebo (N= 200)
Baseline
Mean (SD) | 13.38 (6.57) | 14.26 (13.94) | 14.66 (11.08) | 16.16 (11.15)
Change from Baseline to Week 4
LS-Means (SE) Difference vs. Placebo (95% CI) P-value [- one-sided p-value.] | -7.60 (0.43) -3.29 (-4.47, -2.10) <0.0001 | -4.31 (0.43) | -8.58 (0.49) -3.04 (-4.40, -1.68) <0.0001 | -5.54 (0.49)
Change from Baseline to Week 12
LS-Means (SE) Difference vs. Placebo (95% CI) P-value | -8.66 (0.58) -3.22 (-4.81, -1.63) <0.0001 | -5.44 (0.59) | -9.72 (0.50) -3.24 (-4.60, -1.88) <0.0001 | -6.48 (0.49)
CI = Confidence Interval, LS-Means = Least Squares Means estimated from a mixed model for repeated measures analysis of covariance, SD = standard deviation, SE = Standard Error

Table 5: Mean Baseline and Mean Change in Severity of Moderate to Severe VMS over 24 hours from Baseline to Weeks 4 and 12 (OASIS 1 and 2)
 | Trial 1 |  | Trial 2
Parameter | LYNKUET 120 mg (N= 199) | Placebo (N= 197) | LYNKUET 120 mg (N= 200) | Placebo (N= 200)
Baseline
Mean (SD) | 2.56 (0.22) | 2.53 (0.23) | 2.53 (0.24) | 2.54 (0.24)
Change from Baseline to Week 4
LS-Means (SE) Difference vs. Placebo (95% CI) P-value [- one-sided p-value.] | -0.73 (0.04) -0.33 (-0.44, -0.23) <0.0001 | -0.40 (0.04) | -0.75 (0.04) -0.22 (-0.34, -0.09) 0.0003 | -0.53 (0.04)
Change from Baseline to Week 12
LS-Means (SE) Difference vs. Placebo (95% CI) P-value | -0.92 (0.05) -0.40 (-0.54, -0.25) <0.0001 | -0.52 (0.05) | -0.91 (0.06) -0.29 (-0.44, -0.14) <0.0001 | -0.62 (0.05)
CI = Confidence Interval, LS-Means = Least Squares Means estimated from a mixed model for repeated measures analysis of covariance, SD = standard deviation, SE = Standard Error

The results in reduction of frequency and severity of moderate to severe vasomotor symptoms were consistent across various patient subgroups such as race, ethnicity, BMI and smoking status.

14.2 Effects on Endometrium in Postmenopausal Women

In all three OASIS trials, endometrial biopsies were performed to evaluate endometrial safety. A total of 477 patients who received elinzanetant 120 mg underwent end-of-treatment endometrial biopsies. Among these, 140 received elinzanetant for up to 52 weeks, 162 received elinzanetant for up to 26 weeks, and 175 received elinzanetant for up to 14 weeks. In addition, 132 women in the placebo arm in OASIS 3 also had end-of-treatment endometrial biopsies.

No endometrial malignancies were identified. One case of endometrial hyperplasia with atypia was identified in OASIS 1 and two cases of endometrial hyperplasia without atypia were seen in OASIS 3. Also, one case of endometrial glandular hyperplastic polyp was identified in OASIS 2. The rate of endometrial abnormalities was 0.8% (4 in 477) in patients who received elinzanetant, in line with the expected background rate.

14.3 Special Safety Study

Ability to Operate Vehicles or Machinery

Driving performance was assessed at 9 hours after bedtime administration of LYNKUET 120 mg and 240 mg (two times the recommended dose) in a randomized, double-blind, placebo-and active-controlled, four-period crossover study in 64 healthy women (mean age 52.1 years) using a computer-based driving simulation. The primary outcome measure was the difference from placebo in the Standard Deviation of Lateral Position (SDLP). Driving performance was evaluated using a validated threshold established in a population with blood alcohol concentration of 0.05%. Although the mean SDLP did not reach the threshold for driving impairment after administration of LYNKUET 120 or 240 mg, compared to placebo, driving ability was impaired in some subjects taking LYNKUET 120 or 240 mg after the initial dose. For a smaller percentage of subjects driving ability was impaired after 5-days of consecutive dosing.

16 HOW SUPPLIED/STORAGE AND HANDLING

16.1 How Supplied

LYNKUET 60 mg capsules are supplied as opaque red, oblong, soft gelatin capsules, marked with white printing of "EZN60." LYNKUET capsules are available in the following package size:

- 60-count carton containing 5 blister cards (5 × 12 capsules) | NDC 50419-475-05

16.2 Storage and Handling

Store at 20°C to 25°C (68°F to 77°F) with excursions permitted from 15°C to 30°C (59°F to 86°F) [see USP Controlled Room Temperature].

For patients requiring a dosage modification (i.e., one 60 mg capsule once daily), instruct them to partially peel back the foil covering of the blister cell exposing only one of the two capsules. Store the remaining capsule in the original blister card in the carton until the next dose.

17 PATIENT COUNSELING INFORMATION

Advise the patient to read the FDA-approved patient labeling (Patient Information).

CNS Depressant Effect and Daytime Impairment

Advise patients who experience somnolence and other nervous system effects to refrain from driving or engaging in hazardous occupations or activities until the effects have resolved [see Warnings and precaution (5.1) and Clinical Studies (14.3)].

Hepatic Transaminase Elevations

Advise patients that bloodwork to evaluate for hepatic functions and injury will be obtained at baseline and three months after initiating therapy.

Advise patients to discontinue LYNKUET immediately and seek medical attention including hepatic laboratory tests if they experience signs or symptoms that may suggest liver injury (new onset fatigue, decreased appetite, nausea, vomiting, pruritus, jaundice, pale feces, dark urine, or abdominal pain). [see Warnings and Precautions (5.2)].

Females of Reproductive Potential

Exclude pregnancy in females of reproductive potential prior to initiating LYNKUET. Advise females of reproductive potential to use effective contraception during treatment with LYNKUET and for two weeks after discontinuing treatment and to discontinue LYNKUET if pregnancy is confirmed [see Warnings and Precautions (5.3) and Use in Specific Populations (8.1, 8.3)].

Risk of Seizures in Patients with History of Seizures

Advise patients to report any history of seizures or conditions that potentially lower the seizure threshold. [see Warnings and Precautions (5.4)].

Important Administration Instructions

Advise patients to take LYNKUET once daily at bedtime with water and swallow capsules whole. Advise patients not to cut, crush or chew capsules [see Dosage and Administration (2.1)].

Instruct patients requiring a dosage modification (i.e., one 60 mg capsule once daily) to partially peel back the foil covering the blister cell to expose only one of the two capsules. Instruct patients to store the remaining capsule in the original blister card in the carton until the next dose [see Storage and Handling (16.2)].

Drug Interactions

Advise patients to report their use of any other prescription or nonprescription medications or dietary supplements [see Drug Interactions (7.1)].

Distributed by:

Bayer HealthCare Pharmaceuticals Inc.
Whippany, NJ 07981 USA

© 2025 Bayer HealthCare Pharmaceuticals Inc.

PATIENT INFORMATION
LYNKUET® (lin kew et')
(elinzanetant)
capsules, for oral use

What is LYNKUET?
LYNKUET is a prescription medicine used to reduce moderate to severe hot flashes (also known as vasomotor symptoms) due to menopause. LYNKUET is not a hormone. Hot flashes are feelings of warmth in the face, neck, and chest, or sudden intense feelings of heat and sweating.

Do not take LYNKUET if you:

- are pregnant.

Before you use LYNKUET, tell your healthcare provider about all of your medical conditions, including if you:

- have liver problems.
- have a history of seizures.
- are pregnant or planning to become pregnant. LYNKUET may harm your unborn baby. Women who can become pregnant should talk to their healthcare provider to exclude pregnancy before starting treatment with LYNKUET and use effective birth control during and for 2 weeks after stopping treatment.

Tell your healthcare provider about all the medicines you take, including prescription and over-the-counter medicines, vitamins, and herbal supplements. LYNKUET may affect the way other medicines work, and other medicines may affect how LYNKUET works. Keep a list of your medicines and show it to your healthcare provider and pharmacist when you get a new medicine.

How should I take LYNKUET?

- Take LYNKUET exactly as your healthcare provider tells you to take it.
- Take 2 LYNKUET capsules by mouth, with or without food, about the same time each day at bedtime.
- Swallow the LYNKUET capsules whole with water. Do not cut, crush, or chew capsules.
- If you miss a dose of LYNKUET at bedtime, take the next dose as scheduled the following day. Do not take more than 2 capsules on the same day to make up for a missed dose.
- If you take certain medicines, your healthcare provider may reduce your dose to 1 LYNKUET capsule. If so, partially peel back the foil of the blister card and leave the remaining capsule inside until your next dose.

What should I avoid while taking LYNKUET?

- Avoid eating grapefruit or drinking grapefruit juice during treatment with LYNKUET.
- LYNKUET may cause you to feel drowsy, if you experience this avoid driving and other hazardous activities until these effects go away. See "What are the possible side effects of LYNKUET?".

What are the possible side effects of LYNKUET?

LYNKUET can cause serious side effects, including:

- Central nervous system (CNS) effects and daytime impairment. LYNKUET can cause difficulty staying awake (somnolence) and other nervous system effects including fatigue, having a spinning feeling (vertigo), dizziness, and feeling faint (presyncope). If you experience these effects, you should not drive or do hazardous activities until these effects go away.
- Increased liver blood test values. LYNKUET may cause increased liver enzymes. Your healthcare provider will do a blood test to check your liver before you start and 3 months after taking LYNKUET. Stop taking LYNKUET and tell your healthcare provider right away if you have the following signs or symptoms that suggest liver problems:

- feeling more tired than you do usually
- decreased appetite
- nausea
- vomiting
- itching

- yellowing of the eyes or skin (jaundice)
- pale feces
- dark urine
- pain in the stomach (abdomen)

- Risk of pregnancy loss. Taking LYNKUET while pregnant may cause loss of pregnancy or stillbirth. If you think you are pregnant, stop taking LYNKUET and tell your healthcare provider right away.
- Risk of seizures in people with a history of seizures. Seek medical attention right away if you have loss of consciousness or seizure.

Common side effects of LYNKUET include:

- headache
- fatigue
- dizziness
- feeling drowsy or sleepy

- stomach (abdominal) pain
- rash
- diarrhea
- muscle spasms

Tell your healthcare provider if you have any side effects that bother you or do not go away. These are not all the possible side effects of LYNKUET.
Call your doctor for medical advice about side effects. You may report side effects to FDA at 1-800-FDA-1088.

How should I store LYNKUET?

- Store LYNKUET at room temperature between 68°F to 77°F (20°C to 25°C).
- Keep LYNKUET and all medicines out of the reach of children.

General information about the safe and effective use of LYNKUET.
Medicines are sometimes prescribed for purposes other than those listed in a Patient Information leaflet. Do not use LYNKUET for a condition for which it was not prescribed. Do not give LYNKUET to other people, even if they have the same symptoms you have. It may harm them. You can ask your pharmacist or healthcare provider for information about LYNKUET that is written for healthcare professionals.

What are the ingredients in LYNKUET?
Active ingredient: elinzanetant
Inactive ingredients: all-rac-α-Tocopherol, caprylocaproyl macrogolglycerides, glycerol monocaprylocaprate, glycerol mono-oleate, and polysorbate 80. The capsule is composed of edible ink, ferric oxide red, ferric oxide yellow, gelatin, sorbitol special-glycerin, and titanium dioxide.

Distributed by Bayer HealthCare Pharmaceuticals Inc., Whippany, NJ 07981 USA
For more information, go to www.lynkuet.com or call 1-888-842-2937.

This Patient Information has been approved by the U.S. Food and Drug Administration.

Issued: 10/2025

PRINCIPAL DISPLAY PANEL - 60 mg Capsule Blister Pack

BAYER

NDC 50419-475-01

Lynkuet®
(elinzanetant) capsules
60 mg per capsule
Rx only

LOT:
EXP:

XXXXXXX
YYYY/MMM

PRINCIPAL DISPLAY PANEL - 60 mg Capsule Blister Pack Carton

NDC 50419-475-05
Rx only

Lynkuet®
(elinzanetant) capsules
60 mg per capsule

60 capsules
5 blister cards of 12 capsules each

BAYER

Swallow capsule whole